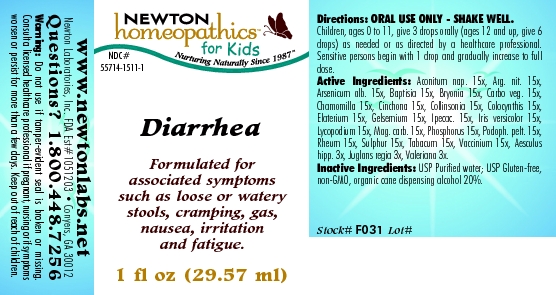 DRUG LABEL: Diarrhea 
NDC: 55714-1511 | Form: LIQUID
Manufacturer: Newton Laboratories, Inc.
Category: homeopathic | Type: HUMAN OTC DRUG LABEL
Date: 20110301

ACTIVE INGREDIENTS: Aconitum Napellus 15 [hp_X]/1 mL; Silver Nitrate 15 [hp_X]/1 mL; Arsenic Trioxide 15 [hp_X]/1 mL; Baptisia Tinctoria 15 [hp_X]/1 mL; Bryonia Alba Root 15 [hp_X]/1 mL; Activated Charcoal 15 [hp_X]/1 mL; Matricaria Recutita 15 [hp_X]/1 mL; Cinchona Officinalis Bark 15 [hp_X]/1 mL; Collinsonia Canadensis Root 15 [hp_X]/1 mL; Citrullus Colocynthis Fruit Pulp 15 [hp_X]/1 mL; Ecballium Elaterium Fruit 15 [hp_X]/1 mL; Gelsemium Sempervirens Root 15 [hp_X]/1 mL; Ipecac 15 [hp_X]/1 mL; Iris Versicolor Root 15 [hp_X]/1 mL; Lycopodium Clavatum Spore 15 [hp_X]/1 mL; Magnesium Carbonate 15 [hp_X]/1 mL; Phosphorus 15 [hp_X]/1 mL; Podophyllum 15 [hp_X]/1 mL; Rheum Officinale Whole 15 [hp_X]/1 mL; Sulfur 15 [hp_X]/1 mL; Tobacco Leaf 15 [hp_X]/1 mL; Bilberry 15 [hp_X]/1 mL; Horse Chestnut 3 [hp_X]/1 mL; Juglans Regia Whole 3 [hp_X]/1 mL; Valerian 3 [hp_X]/1 mL
INACTIVE INGREDIENTS: Alcohol

Diarrhea

INDICATIONS & USAGE SECTION

Diarrhea Formulated for associated symptoms such as loose or watery stools, cramping, gas, nausea, irritation and fatigue.

DOSAGE & ADMINISTRATION SECTION

Directions: ORAL USE ONLY - SHAKE WELL. Children, ages 0 to 11, give 3 drops orally (ages 12 and up, give 6 drops) as needed or as directed by a healthcare professional. Sensitive persons begin with 1 drop and gradually increase to full dose.

OTC - ACTIVE INGREDIENT SECTION

Aconitum nap. 15x, Arg. nit. 15x, Arsenicum alb. 15x, Baptisia 15x, Bryonia 15x, Carbo veg. 15x, Chamomilla 15x, Cinchona 15x, Collinsonia 15x, Colocynthis 15x, Elaterium 15x, Gelsemium 15x, Ipecac. 15x, Iris versicolor 15x, Lycopodium 15x, Mag. carb. 15x, Phosphorus 15x, Podoph. pelt. 15x, Rheum 15x, Sulphur 15x, Tabacum 15x, Vaccinium 15x, Aesculus hipp. 3x, Juglans regia 3x, Valeriana 3x.

OTC - PURPOSE SECTION

Formulated for associated symptoms such as loose or watery stools, cramping, gas, nausea, irritation and fatigue.

INACTIVE INGREDIENT SECTION

Inactive Ingredients: USP Purified Water; USP Gluten-free, non-GMO, organic cane dispensing alcohol 20%.

QUESTIONS SECTION

www.newtonlabs.net Newton Laboratories, Inc. FDA Est # 1051203 - Conyers, GA 30012
Questions? 1.800.448.7256

WARNINGS SECTION

Warning: Do not use if tamper - evident seal is broken or missing. Consult a licensed healthcare professional if pregnant, nursing or if symptoms worsen or persist for more than a few days. Keep out of reach of children.

OTC - PREGNANCY OR BREAST FEEDING SECTION

Consult a licensed healthcare professional if pregnant, nursing or if symptoms worsen or persist for more than a few days.

OTC - KEEP OUT OF REACH OF CHILDREN SECTION

Keep out of reach of children.